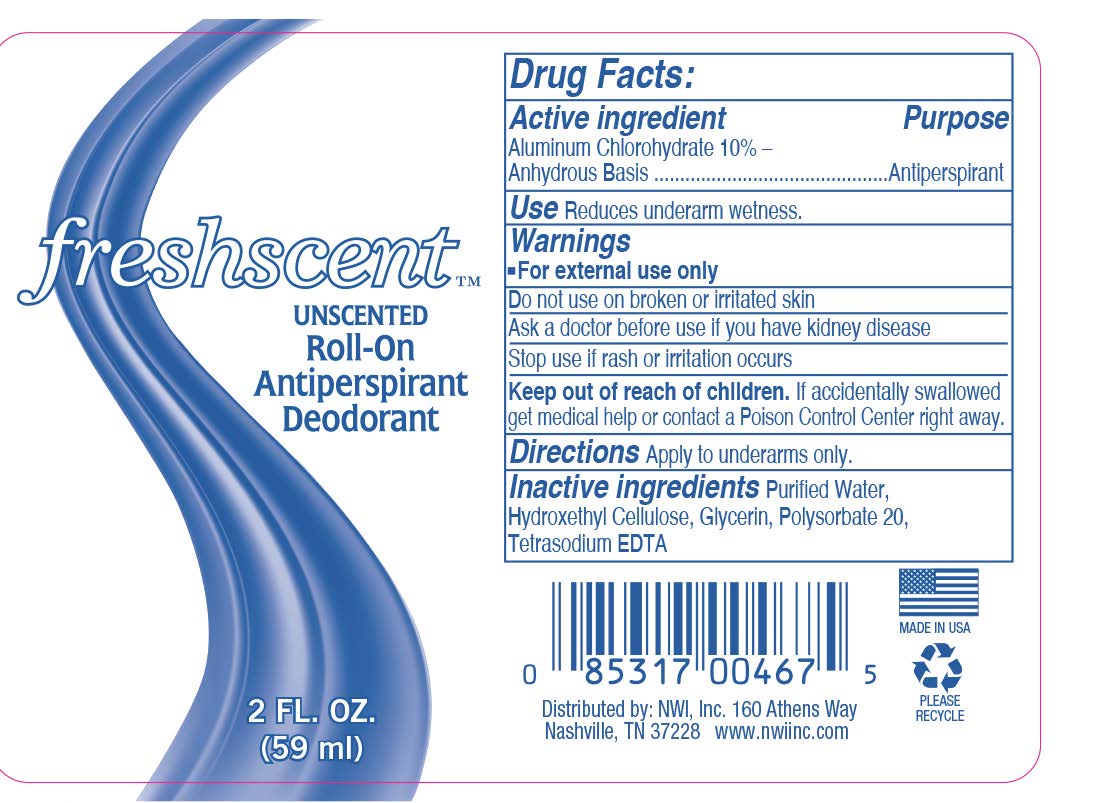 DRUG LABEL: Freshscent Anti-Perspirant Deodorant
NDC: 51824-022 | Form: SOLUTION
Manufacturer: New World Imports, Inc.
Category: otc | Type: HUMAN OTC DRUG LABEL
Date: 20260112

ACTIVE INGREDIENTS: ALUMINUM CHLOROHYDRATE 10 g/100 mL
INACTIVE INGREDIENTS: WATER; HYDROXYETHYL CELLULOSE, UNSPECIFIED; GLYCERIN; POLYSORBATE 20; TETRASODIUM EDETATE DIHYDRATE

Anti-Perspirant Deodorant

Drug Facts

Active ingredient

Aluminum Chlorohydrate 10% –
Anhydrous Basis

Purpose

Antiperspirant

Use

Reduces underarm wetness.

Warnings

For external use only.

Keep out of reach of children. If accidentally swallowed get medical help or contact a Poison Control Center right away.

Do not use on broken or irritated skin.

Stop use if rash or irritation occurs.

Ask a doctor before use if you have kidney disease.

Directions

Apply to underarms only.

Inactive ingredients

Purified Water, Hydroxyethylcellulose, Glycerin, Polysorbate 20, Tetrasodium EDTA